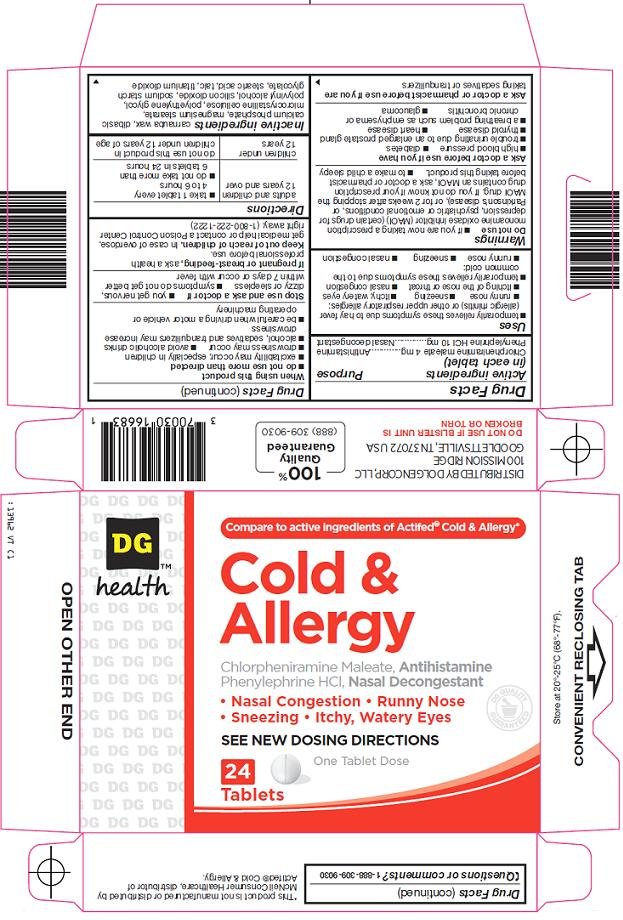 DRUG LABEL: DG Health Cold and Allergy
NDC: 55910-139 | Form: TABLET, FILM COATED
Manufacturer: Dolgencorp Inc
Category: otc | Type: HUMAN OTC DRUG LABEL
Date: 20091130

ACTIVE INGREDIENTS: CHLORPHENIRAMINE MALEATE 4 mg/1 1; PHENYLEPHRINE HYDROCHLORIDE 10 mg/1 1

Dolgencorp, LLC Cold & Allergy Drug Facts

Active ingredient (in each tablet)

Chlorpheniramine maleate 4 mg

Phenylephrine HCl 10 mg

Purpose

Antihistamine

Nasal decongestant

Uses

- temporarily relieves these symptoms due to hay fever (allergic rhinitis) or other upper respiratory allergies:
- runny nose
- sneezing
- itchy, watery eyes
- nasal congestion
- itching of the nose or throat
- temporarily relieves these symptoms due to the common cold:
- runny nose
- sneezing
- nasal congestion

Warnings

Do not use

- if you are now taking a prescription monoamine oxidase inhibitor (MAOI) (certain drugs for depression, psychiatric or emotional conditions, or Parkinson’s disease), or for 2 weeks after stopping the MAOI drug. If you do not know if your prescription drug contains an MAOI, ask a doctor or pharmacist before taking this product.
- to make a child sleepy

Ask a doctor before use if you have

- heart disease
- high blood pressure
- thyroid disease
- diabetes
- trouble urinating due to an enlarged prostate gland
- a breathing problem such as emphysema or chronic bronchitis
- glaucoma

Ask a doctor or pharmacist before use if you are

taking sedatives or tranquilizers

When using this product

- do not use more than directed
- excitability may occur, especially in children
- drowsiness may occur
- alcohol, sedatives and tranquilizers may increase drowsiness
- avoid alcoholic drinks
- be careful when driving a motor vehicle or operating machinery

Stop use and ask a doctor if

- you get nervous, dizzy or sleepless
- symptoms do not get better within 7 days or occur with fever

If pregnant or breast-feeding,

ask a health professional before use.

Keep out of reach of children.

In case of overdose, get medical help or contact a Poison Control Center right away. (1-800-222-1222)

Directions

adults and children 12 years and over | - take 1 tablet every 4 to 6 hours - do not take more than 6 tablets in 24 hours
children under 12 years | do not use this product in children under 12 years of age

Inactive ingredients

carnauba wax, dibasic calcium phosphate, magnesium stearate, microcrystalline cellulose, polyethylene glycol, polyvinyl alcohol, silicon dioxide, sodium starch glycolate, stearic acid, talc, titanium dioxide

Questions or comments?

1-888-309-9030

Principal Display Panel

Compare to active ingredients of Actifed® Cold & Allergy

Cold & Allergy

Chlorpheniramine Maleate, Antihistamine

Phenylephrine HCl, Nasal Decongestant

Nasal Congestion

Runny Nose

Sneezing

Itchy, Watery Eyes

See New Dosing Directions

One Tablet Dose

Cold & Allergy Carton